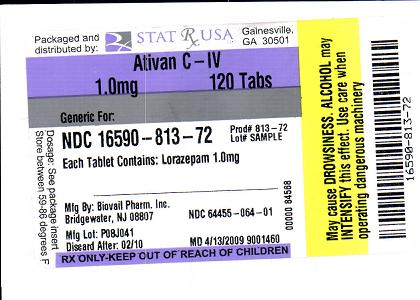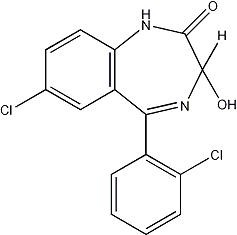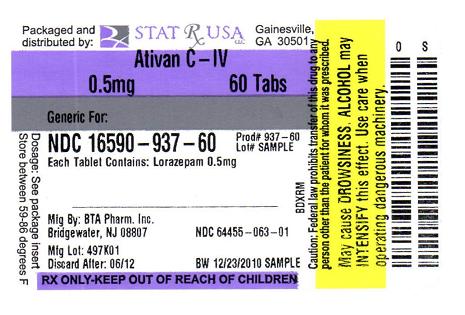 DRUG LABEL: ATIVAN
NDC: 16590-813 | Form: TABLET
Manufacturer: STAT RX USA LLC
Category: prescription | Type: HUMAN PRESCRIPTION DRUG LABEL
Date: 20110208
DEA Schedule: CIV

ACTIVE INGREDIENTS: LORAZEPAM 1 mg/1 1
INACTIVE INGREDIENTS: LACTOSE MONOHYDRATE; MAGNESIUM STEARATE; CELLULOSE, MICROCRYSTALLINE; POLACRILIN POTASSIUM

Rx only

DESCRIPTION

Ativan (lorazepam), an antianxiety agent, has the chemical formula, 7-chloro-5-(o-chlorophenyl)-1,3-dihydro-3-hydroxy-2H-1,4-benzodiazepin-2-one:

It is a nearly white powder almost insoluble in water. Each Ativan (lorazepam) tablet, to be taken orally, contains 0.5 mg, 1 mg, or 2 mg of lorazepam. The inactive ingredients present are lactose monohydrate, magnesium stearate, microcrystalline cellulose, and polacrilin potassium.

CLINICAL PHARMACOLOGY

Studies in healthy volunteers show that in single high doses Ativan (lorazepam) has a tranquilizing action on the central nervous system with no appreciable effect on the respiratory or cardiovascular systems.

Ativan (lorazepam) is readily absorbed with an absolute bioavailability of 90 percent. Peak concentrations in plasma occur approximately 2 hours following administration. The peak plasma level of lorazepam from a 2 mg dose is approximately 20 ng/mL.

The mean half-life of unconjugated lorazepam in human plasma is about 12 hours and for its major metabolite, lorazepam glucuronide, about 18 hours. At clinically relevant concentrations, lorazepam is approximately 85% bound to plasma proteins. Ativan (lorazepam) is rapidly conjugated at its 3-hydroxy group into lorazepam glucuronide which is then excreted in the urine. Lorazepam glucuronide has no demonstrable CNS activity in animals.

The plasma levels of lorazepam are proportional to the dose given. There is no evidence of accumulation of lorazepam on administration up to six months.

Studies comparing young and elderly subjects have shown that advancing age does not have a significant effect on the pharmacokinetics of lorazepam. However, in one study involving single intravenous doses of 1.5 to 3 mg of Ativan Injection, mean total body clearance of lorazepam decreased by 20% in 15 elderly subjects of 60 to 84 years of age compared to that in 15 younger subjects of 19 to 38 years of age.

INDICATIONS AND USAGE

Ativan (lorazepam) is indicated for the management of anxiety disorders or for the short-term relief of the symptoms of anxiety or anxiety associated with depressive symptoms. Anxiety or tension associated with the stress of everyday life usually does not require treatment with an anxiolytic.

The effectiveness of Ativan (lorazepam) in long-term use, that is, more than 4 months, has not been assessed by systematic clinical studies. The physician should periodically reassess the usefulness of the drug for the individual patient.

CONTRAINDICATIONS

Ativan (lorazepam) is contraindicated in patients with
– hypersensitivity to benzodiazepines or to any components of the formulation.
– acute narrow-angle glaucoma.

WARNINGS

Pre-existing depression may emerge or worsen during use of benzodiazepines including lorazepam. Ativan (lorazepam) is not recommended for use in patients with a primary depressive disorder or psychosis.

Use of benzodiazepines, including lorazepam, both used alone and in combination with other CNS depressants, may lead to potentially fatal respiratory depression. (See PRECAUTIONS Clinically Significant Drug Interactions)

Use of benzodiazepines, including lorazepam, may lead to physical and psychological dependence.

As with all patients on CNS- depressant drugs, patients receiving lorazepam should be warned not to operate dangerous machinery or motor vehicles and that their tolerance for alcohol and other CNS depressants will be diminished.

Physical and Psychological Dependence

The use of benzodiazepines, including lorazepam, may lead to physical and psychological dependence. The risk of dependence increases with higher doses and longer term use and is further increased in patients with a history of alcoholism or drug abuse or in patients with significant personality disorders. The dependence potential is reduced when lorazepam is used at the appropriate dose for short-term treatment. Addiction-prone individuals (such as drug addicts or alcoholics) should be under careful surveillance when receiving lorazepam or other psychotropic agents.

In general, benzodiazepines should be prescribed for short periods only (e.g., 2 to 4 weeks). Extension of the treatment period should not take place without reevaluation of the need for continued therapy. Continuous long-term use of product is not recommended. Withdrawal symptoms (e.g., rebound insomnia) can appear following cessation of recommended doses after as little as one week of therapy. Abrupt discontinuation of product should be avoided and a gradual dosage-tapering schedule followed after extended therapy.

Abrupt termination of treatment may be accompanied by withdrawal symptoms. Symptoms reported following discontinuation of benzodiazepines include headache, anxiety, tension, depression, insomnia, restlessness, confusion, irritability, sweating, rebound phenomena, dysphoria, dizziness, derealization, depersonalization, hyperacusis, numbness/tingling of extremities, hypersensitivity to light, noise, and physical contact/perceptual changes, involuntary movements, nausea, vomiting, diarrhea, loss of appetite, hallucinations/delirium, convulsions/seizures, tremor, abdominal cramps, myalgia, agitation, palpitations, tachycardia, panic attacks, vertigo, hyperreflexia, short-term memory loss, and hyperthermia. Convulsions/seizures may be more common in patients with pre-existing seizure disorders or who are taking other drugs that lower the convulsive threshold such as antidepressants.

There is evidence that tolerance develops to the sedative effects of benzodiazepines.

Lorazepam may have abuse potential, especially in patients with a history of drug and/or alcohol abuse.

PRECAUTIONS

In patients with depression, a possibility for suicide should be borne in mind; benzodiazepines should not be used in such patients without adequate anti-depressant therapy.

Lorazepam should be used with caution in patients with compromised respiratory function (e.g., COPD, sleep apnea syndrome).

Elderly or debilitated patients may be more susceptible to the sedative effects of lorazepam. Therefore, these patients should be monitored frequently and have their dosage adjusted carefully according to patient response; the initial dosage should not exceed 2 mg.

Paradoxical reactions have been occasionally reported during benzodiazepine use. Such reactions may be more likely to occur in children and the elderly. Should these occur, use of the drug should be discontinued.

The usual precautions for treating patients with impaired renal or hepatic function should be observed. As with all benzodiazepines, the use of lorazepam may worsen hepatic encephalopathy; therefore, lorazepam should be used with caution in patients with severe hepatic insufficiency and/or encephalopathy. Dosage for patients with severe hepatic insufficiency should be adjusted carefully according to patient response; lower doses may be sufficient in such patients.

In patients where gastrointestinal or cardiovascular disorders coexist with anxiety, it should be noted that lorazepam has not been shown to be of significant benefit in treating the gastrointestinal or cardiovascular component.

Esophageal dilation occurred in rats treated with lorazepam for more than one year at 6 mg/kg/day. The no-effect dose was 1.25 mg/kg/day (approximately 6 times the maximum human therapeutic dose of 10 mg per day). The effect was reversible only when the treatment was withdrawn within two months of first observation of the phenomenon. The clinical significance of this is unknown. However, use of lorazepam for prolonged periods and in geriatric patients requires caution, and there should be frequent monitoring for symptoms of upper G.I. disease.

Safety and effectiveness of Ativan (lorazepam) in children of less than 12 years have not been established.

Information for Patients

To assure the safe and effective use of Ativan (lorazepam), patients should be informed that, since benzodiazepines may produce psychological and physical dependence, it is advisable that they consult with their physician before either increasing the dose or abruptly discontinuing this drug.

Essential Laboratory Tests

Some patients on Ativan (lorazepam) have developed leukopenia, and some have had elevations of LDH. As with other benzodiazepines, periodic blood counts and liver-function tests are recommended for patients on long-term therapy.

Clinically Significant Drug Interactions

The benzodiazepines, including Ativan (lorazepam), produce increased CNS-depressant effects when administered with other CNS depressants such as alcohol, barbiturates, antipsychotics, sedative/hypnotics, anxiolytics, antidepressants, narcotic analgesics, sedative antihistamines, anticonvulsants, and anesthetics.

Concomitant use of clozapine and lorazepam may produce marked sedation, excessive salivation, hypotension, ataxia, delirium, and respiratory arrest.

Concurrent administration of lorazepam with valproate results in increased plasma concentrations and reduced clearance of lorazepam. Lorazepam dosage should be reduced to approximately 50% when coadministered with valproate.

Concurrent administration of lorazepam with probenecid may results in a more rapid onset or prolonged effect of lorazepam due to increased half-life and decreased total clearance. Lorazepam dosage needs to be reduced by approximately 50% when coadministered with probenecid.

The effects of probenecid and valproate on lorazepam may be due to inhibition of glucuronidation.

Administration of theophylline or aminophylline may reduce the sedative effects of benzodiazepines, including lorazepam.

Carcinogenesis and Mutagenesis

No evidence of carcinogenic potential emerged in rats during an 18-month study with Ativan (lorazepam). No studies regarding mutagenesis have been performed.

Pregnancy

Reproductive studies in animals were performed in mice, rats, and two strains of rabbits. Occasional anomalies (reduction of tarsals, tibia, metatarsals, malrotated limbs, gastroschisis, malformed skull, and microphthalmia) were seen in drug-treated rabbits without relationship to dosage. Although all of these anomalies were not present in the concurrent control group, they have been reported to occur randomly in historical controls. At doses of 40 mg/kg and higher, there was evidence of fetal resorption and increased fetal loss in rabbits which was not seen at lower doses.

The clinical significance of the above findings is not known. However, an increased risk of congenital malformations associated with the use of minor tranquilizers (chlordiazepoxide, diazepam, and meprobamate) during the first trimester of pregnancy has been suggested in several studies. Because the use of these drugs is rarely a matter of urgency, the use of lorazepam during this period should be avoided. The possibility that a woman of childbearing potential may be pregnant at the time of institution of therapy should be considered. Patients should be advised that if they become pregnant, they should communicate with their physician about the desirability of discontinuing the drug.

In humans, blood levels obtained from umbilical cord blood indicate placental transfer of lorazepam and lorazepam glucuronide. Infants of mothers who ingested benzodiazepines for several weeks or more preceding delivery have been reported to have withdrawal symptoms during the postnatal period. Symptoms such as hypoactivity, hypotonia, hypothermia, respiratory depression, apnea, feeding problems, and impaired metabolic response to cold stress have been reported in neonates born of mothers who have received benzodiazepines during the late phase of pregnancy or at delivery.

Nursing Mothers

Lorazepam has been detected in human breast milk; therefore, it should not be administered to breast-feeding women, unless the expected benefit to the woman outweighs the potential risk to the infant.

Sedation and inability to suckle have occurred in neonates of lactating mothers taking benzodiazepines. Infants of lactating mothers should be observed for pharmacological effects (including sedation and irritability).

Geriatric Use

Clinical studies of Ativan generally were not adequate to determine whether subjects aged 65 and over respond differently than younger subjects; however, the incidence of sedation and unsteadiness was observed to increase with age (see ADVERSE REACTIONS).

Age does not appear to have a significant effect on lorazepam kinetics (see CLINICAL PHARMACOLOGY).

Clinical circumstances, some of which may be more common in the elderly, such as hepatic or renal impairment, should be considered. Greater sensitivity (e.g., sedation) of some older individuals cannot be ruled out. In general, dose selection for an elderly patient should be cautious, and lower doses may be sufficient in these patients (see DOSAGE AND ADMINISTRATION).

ADVERSE REACTIONS

Most adverse reactions to benzodiazepines, including CNS effects and respiratory depression, are dose dependent, with more severe effects occurring with high doses.

In a sample of about 3500 patients treated for anxiety, the most frequent adverse reaction to Ativan (lorazepam) was sedation (15.9%), followed by dizziness (6.9%), weakness (4.2%), and unsteadiness (3.4%). The incidence of sedation and unsteadiness increased with age.

Other adverse reactions to benzodiazepines, including lorazepam are fatigue, drowsiness, amnesia, memory impairment, confusion, disorientation, depression, unmasking of depression, disinhibition, euphoria, suicidal ideation/attempt, ataxia, asthenia, extrapyramidal symptoms, convulsions/seizures tremor, vertigo, eye-function/visual disturbance (including diplopia and blurred vision), dysarthria/slurred speech, change in libido, impotence, decreased orgasm; headache, coma; respiratory depression, apnea, worsening of sleep apnea, worsening of obstructive pulmonary disease; gastrointestinal symptoms including nausea, change in appetite, constipation, jaundice, increase in bilirubin, increase in liver transaminases, increase in alkaline phosphatase; hypersensitivity reactions, anaphylactic/oid reactions; dermatological symptoms, allergic skin reactions, alopecia; SIADH, hyponatremia; thrombocytopenia, agranulocytosis, pancytopenia; hypothermia; and autonomic manifestations.

Paradoxical reactions, including anxiety, excitation, agitation, hostility, aggression, rage, sleep disturbances/insomnia, sexual arousal, and hallucinations may occur. Small decreases in blood pressure and hypotension may occur but are usually not clinically significant, probably being related to the relief of anxiety produced by Ativan (lorazepam).

OVERDOSAGE

In postmarketing experience, overdose with lorazepam has occurred predominantly in combination with alcohol and/or other drugs. Therefore, in the management of overdosage, it should be borne in mind that multiple agents may have been taken.

Symptoms

Overdosage of benzodiazepines is usually manifested by varying degrees of central nervous system depression ranging from drowsiness to coma. In mild cases, symptoms include drowsiness, mental confusion, paradoxical reactions, dysarthria and lethargy. In more serious cases, and especially when other drugs or alcohol were ingested, symptoms may include ataxia, hypotonia, hypotension, cardiovascular depression, respiratory depression, hypnotic state, coma, and, death.

Management

General supportive and symptomatic measures are recommended; vital signs must be monitored and the patient closely observed. When there is a risk of aspiration, induction of emesis is not recommended. Gastric lavage may be indicated if performed soon after ingestion or in symptomatic patients. Administration of activated charcoal may also limit drug absorption. Hypotension, though unlikely, usually may be controlled with norepinephrine bitartrate injection. Lorazepam is poorly dialyzable. Lorazepam glucuronide, the inactive metabolite, may be highly dialyzable.

The benzodiazepine antagonist flumazenil may be used in hospitalized patients as an adjunct to, not as a substitute for, proper management of benzodiazepine overdose. The prescriber should be aware of a risk of seizure in association with flumazenil treatment, particularly in long-term benzodiazepine users and in cyclic antidepressant overdose. The complete flumazenil package insert including CONTRAINDICATIONS, WARNINGS, and PRECAUTIONS should be consulted prior to use.

DOSAGE AND ADMINISTRATION

Ativan (lorazepam) is administered orally. For optimal results, dose, frequency of administration, and duration of therapy should be individualized according to patient response. To facilitate this, 0.5 mg, 1 mg, and 2 mg tablets are available.

The usual range is 2 to 6 mg/day given in divided doses, the largest dose being taken before bedtime, but the daily dosage may vary from 1 to 10 mg/day.

For anxiety, most patients require an initial dose of 2 to 3 mg/day given b.i.d. or t.i.d.

For insomnia due to anxiety or transient situational stress, a single daily dose of 2 to 4 mg may be given, usually at bedtime.

For elderly or debilitated patients, an initial dosage of 1 to 2 mg/day in divided doses is recommended, to be adjusted as needed and tolerated.

The dosage of Ativan (lorazepam) should be increased gradually when needed to help avoid adverse effects. When higher dosage is indicated, the evening dose should be increased before the daytime doses.

HOW SUPPLIED

Ativan® (lorazepam) Tablets are available in the following dosage strengths:

0.5 mg, white, five-sided (shield shape) tablet with a raised "A" on one side and "BPI" and "63" impressed on reverse side.
NDC 64455-063-01 - Bottles of 100 tablets

1 mg, white, five-sided (shield shape) tablet with a raised "A" on one side and "BPI" and "64" impressed on scored reverse side.
NDC 64455-064-01 - Bottles of 100 tablets
NDC 64455-064-10 - Bottles of 1000 tablets

2 mg, white, five-sided (regular pentagon) tablet with a raised "A" and impressed "2" on one side and "BPI" and "65" impressed on scored reverse side.
NDC 64455-065-01 - Bottles of 100 tablets

BOTTLES:

Keep tightly closed.

Store at 25°C (77°F); excursions permitted to 15 - 30° (59 – 86°F) [see USP Controlled Room Temperature].

Dispense in a tight container.

Manufactured by:
MEDA Manufacturing GmbH
Cologne, Germany D-51063

For:
BTA Pharmaceuticals, Inc.
(subsidiary of Biovail Corporation)
Bridgewater, NJ, 08807, USA

Tablets made in Germany

Ativan® is a registered trademark of Biovail Laboratories International SRL.

LB0057-02
Rev. 10/09

ATIVAN 1 MG TAB PACKAGE LABEL

ATIVAN 0.5 MG TAB PACKAGE LABEL